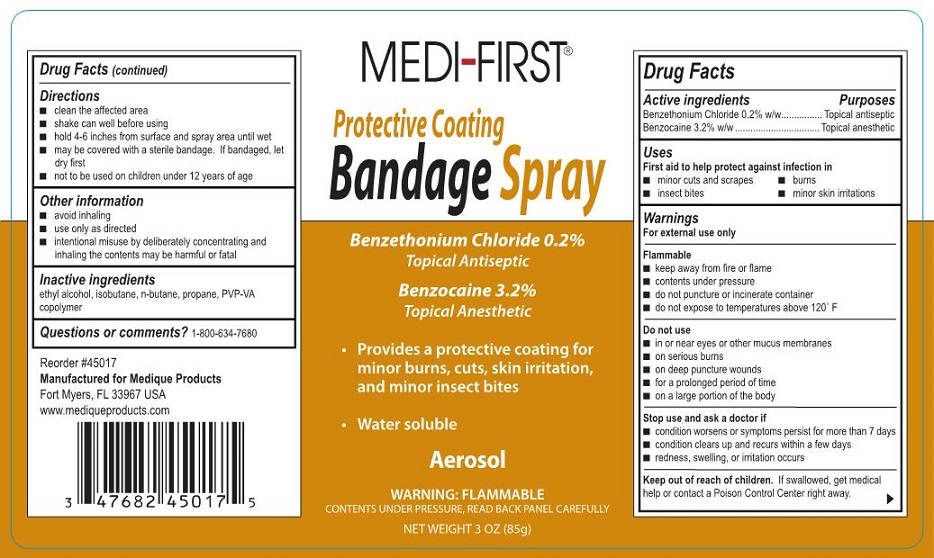 DRUG LABEL: Medi-first Protective Coating Bandage
NDC: 47682-450 | Form: AEROSOL, SPRAY
Manufacturer: Unifirst First Aid Corporation
Category: otc | Type: HUMAN OTC DRUG LABEL
Date: 20250908

ACTIVE INGREDIENTS: BENZETHONIUM CHLORIDE 170 mg/85 g; BENZOCAINE 2720 mg/85 g
INACTIVE INGREDIENTS: ISOBUTANE; ALCOHOL; BUTANE; PROPANE; COPOVIDONE K25-31

Medi-First Bandage Spray

Active ingredients

Benzethonium Chloride 0.2% w/w
Benzocaine 3.2% w/w

Purpose

Topical antiseptic
Topical anesthetic

Uses

First aid to help protect against infection in

- minor cuts and scrapes
- burns

Warnings

For external use only

Flammable

- keep away from fire or flame
- contents under pressure
- do not puncture or incinerate container
- do not expose to temperatures above 120° F

Do not use

- in or near eyes or other mucus membranes
- in case of serious burns
- in case of deep or puncture wounds
- for a prolonged period of time
- on a large portion of the body

Stop use and ask a doctor if

- condition worsens or symptoms persist for more than 7 days
- condition clears up and recurs within a few days
- redness, swelling, or irritation occurs

Keep out of reach of children.

If swallowed, get medical help or contact a Poison Control Center right away.

Directions

- clean the affected area
- shake can well before using
- hold 4-6 inches from surface and spray area until wet
- may be covered with sterile bandage. If bandaged, let dry first
- for adult institutional use only
- not intended for use on children

Other information

- avoid inhaling
- use only as directed
- intentional misuse by deliberately concentrating and inhaling contents may be harmful or fatal

Inactive ingredients

Ethyl alcohol, isobutane, n-butane, propane, PVP-VA copolymer

Questions or comments?

1-800-634-7680

Medi-First Bandage Spray Label

Medi-First®

Protective Coating

Bandage Spray

Benzethonium Chloride 0.2%

Topical Antiseptic

Benzocaine 3.2%
Topical Ansthetic

- Provides a protective coating for minor burns, cuts, skin irritation, and minor insect bites
- Water soluble

Aerosol

WARNING:FLAMMABLE

Contents Under Pressure, Read Back Panel Carefully

Net Weight 3 OZ (85g)